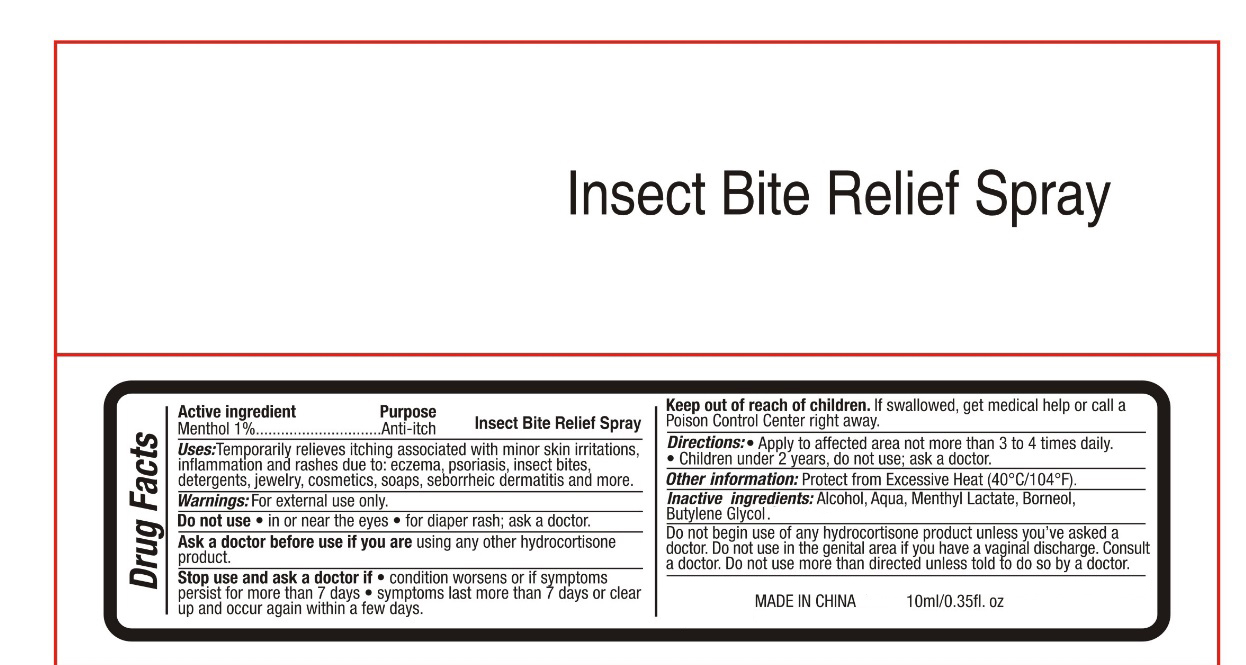 DRUG LABEL: insect bite relief
NDC: 82953-026 | Form: SPRAY
Manufacturer: Cosmuses Cosmetics (Ningbo) Co., Ltd.
Category: otc | Type: HUMAN OTC DRUG LABEL
Date: 20240923

ACTIVE INGREDIENTS: MENTHOL 1 g/100 mL
INACTIVE INGREDIENTS: WATER; MENTHYL LACTATE, (-)-; BORNEOL; BUTYLENE GLYCOL; ALCOHOL

insect bites relief spray (update 240921)

Active Ingredients

Menthol 1%

Purpose

Anti-itch

Insect bite relief spray

Uses

Temporarily relieves itching associated with minor skin irritations, inflammation and rashes due to: eczema, psoriasis, insect bites, detergents, jewelry, cosmetics, soaps, seborrheic dermatitis and more.

Warnings

For external use only.

Do not use

- in or near the eyes
- for disper rash; ask a doctor

Ask a doctor before use if you are using any other hydrocortisone product.

Stop use and ask a doctor if

- condition worsens or if symptoms persist for more than 7 days
- symptoms last more than 7 days or clear up and occur again within a few days

Keep out of reach of children. If swallowed, get medical help or contact a Poison Control Center right away.

Directions

- Apply to affected area not more than 3 to 4 times daily.
- Children under 2 years, do not use; ask a doctor.

Other information

Protect from excessive heat (40oC/ 104oF)

Inactive ingredients

Alcohol, Aqua, Menthyl Lactate, Borneol, Butylene Glycol.

INDICATIONS AND USAGE

Do not begin use of any hydrocortisone product unless you've asked a doctor. Do not use in the genital area if you have a vaginal discharge. Consult a doctor. Do not use more than directed unless told to do so by a doctor.